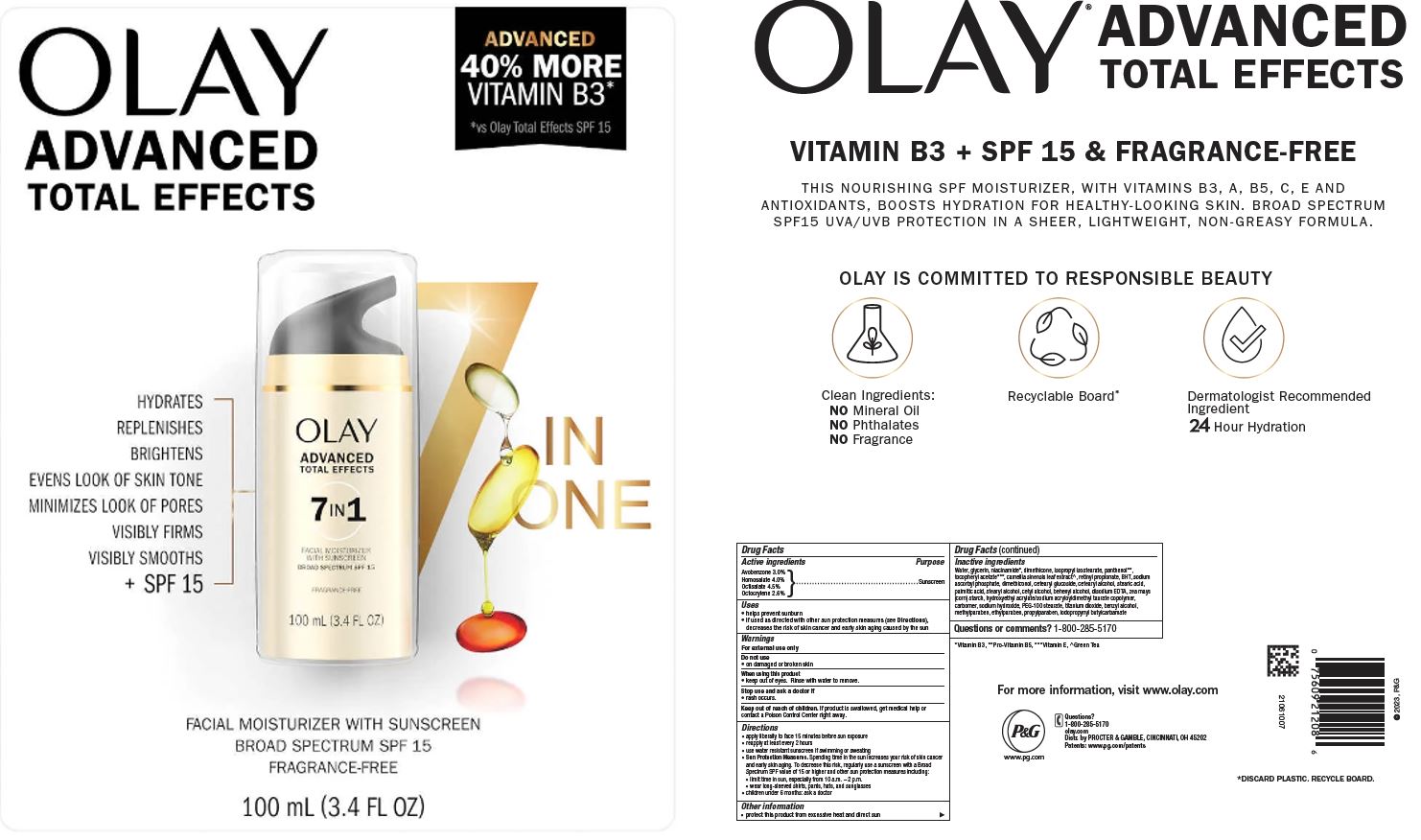 DRUG LABEL: Olay Total Effects Advanced Facial Moisturizer with Sunscreen
NDC: 84126-033 | Form: LOTION
Manufacturer: The Procter & Gamble Manufacturing Company
Category: otc | Type: HUMAN OTC DRUG LABEL
Date: 20251231

ACTIVE INGREDIENTS: AVOBENZONE 3 g/100 mL; HOMOSALATE 4 g/100 mL; OCTISALATE 4.5 g/100 mL; OCTOCRYLENE 2.6 g/100 mL
INACTIVE INGREDIENTS: RETINYL PROPIONATE; DIMETHICONOL (50000 CST); HYDROXYETHYL ACRYLATE/SODIUM ACRYLOYLDIMETHYL TAURATE COPOLYMER (100000 MPA.S AT 1.5%); CARBOXYPOLYMETHYLENE; PALMITIC ACID; BENZYL ALCOHOL; CETOSTEARYL ALCOHOL; WATER; GLYCERIN; NIACINAMIDE; DIMETHICONE; ISOPROPYL ISOSTEARATE; PANTHENOL; .ALPHA.-TOCOPHEROL ACETATE; TITANIUM DIOXIDE; STEARYL ALCOHOL; DOCOSANOL; CETYL ALCOHOL; METHYLPARABEN; PEG-100 STEARATE; ETHYLPARABEN; PROPYLPARABEN; SODIUM HYDROXIDE; SODIUM ASCORBYL PHOSPHATE; CETEARYL GLUCOSIDE; STEARIC ACID; BUTYLATED HYDROXYTOLUENE; EDETATE DISODIUM; IODOPROPYNYL BUTYLCARBAMATE; GREEN TEA LEAF; STARCH, TAPIOCA; STARCH, CORN

Olay® Total Effects® Moisturizer
Broad Spectrum SPF 15 Fragrance Free

Drug Facts

ACTIVE INGREDIENT

Avobenzone 3.0%
Homosalate 4.0%
Octisalate 4.5%
Octocrylene 2.6%

PURPOSE

Sunscreen

Uses

- helps prevent sunburn
- if used as directed with other sun protection measures (see Directions), decreases the risk of skin cancer and early skin aging caused by the sun

Warnings

For external use only

Do not use

- on damaged or broken skin

When using this product

- keep out of eyes. Rinse with water to remove.

Stop use and ask a doctor if

- rash occurs

Keep out of reach of children. If product is swallowed, get medical help or contact a Poison Control Center right away.

Directions

- apply liberally 15 minutes before sun exposure
- reapply at least every 2 hours
- use water resistant sunscreen if swimming or sweating
- Sun Protection Measures. Spending time in the sun increases your risk of skin cancer and early skin aging. To decrease this risk, regularly use a sunscreen with a Broad Spectrum SPF value of 15 or higher and other sun protection measures including:
  - limit time in sun, especially from 10 a.m. - 2 p.m.
  - wear long-sleeved shirts, pants, hats, and sunglasses
- children under 6 months: ask a doctor

Other information

- protect this product from excessive heat and direct sun

Inactive ingredients

Water, glycerin, niacinamide, dimethicone, isopropyl isostearate, panthenol, tocopheryl acetate, camellia sinensis leaf extract, retinyl propionate, BHT, sodium ascorbyl phosphate, dimethiconol, cetearyl glucoside, cetearyl alcohol, stearic acid, palmitic acid, stearyl alcohol, cetyl alcohol, behenyl alcohol, disodium EDTA, zea mays (corn) starch, hydroxyethyl acrylate/sodium acryloyldimethyl taurate copolymer, carbomer, sodium hydroxide, PEG-100 stearate, titanium dioxide, benzyl alcohol, methylparaben, ethylparaben, propylparaben, iodopropynyl butylcarbamate

Questions or comments?

Call 1-800-285-5170

Distr. by PROCTER & GAMBLE,
CINCINNATI, OH 45202

PRINCIPAL DISPLAY PANEL - 100 mL Blister Card

OLAY

ADVANCED

TOTAL EFFECTS

FACIAL MOISTURIZER WITH SUNSCREEN

BROAD SPECTRUM SPF 15
FRAGRANCE-FREE

100 mL (3.4 FL OZ)